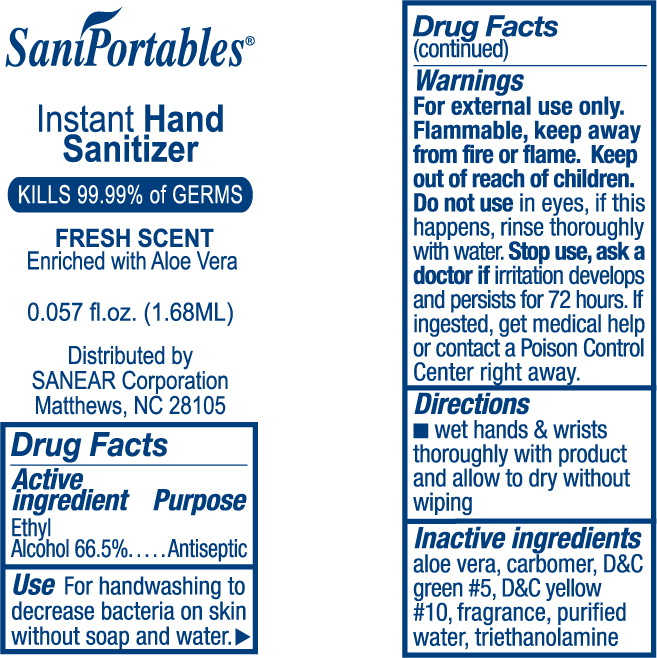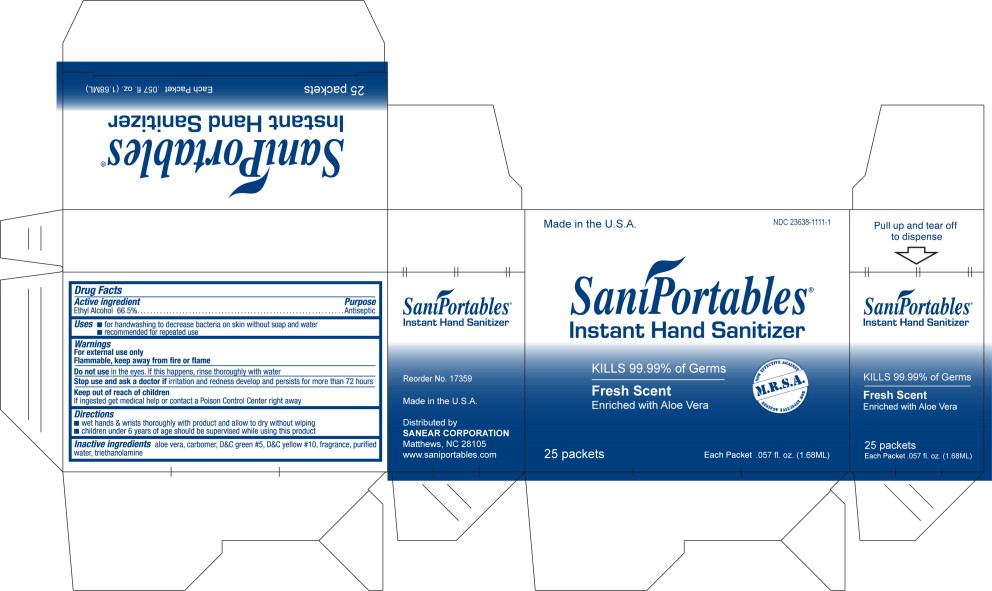 DRUG LABEL: Instant Hand Sanitizer
NDC: 23638-1111 | Form: GEL
Manufacturer: Sanear Corporation
Category: otc | Type: HUMAN OTC DRUG LABEL
Date: 20111121

ACTIVE INGREDIENTS: alcohol 665 mL/1 L
INACTIVE INGREDIENTS: aloe; water; trolamine

Instant Hand Sanitizer

Drug Facts

Active ingredient

Ethyl Alcohol 66.5%

Purpose

Antiseptic

Use

For handwashing to decrease bacteria on skin without soap and water.

Warnings

For external use only.

Flammable, keep away from fire or flame.

Keep out of reach of children.

Do not use in eyes, if this happens, rinse thoroughly with water.

Stop use, ask a doctor If irritation develops and persists for 72 hours. If ingested, get medical help or contact a Poison Control Center right away.

Directions

- wet hands & wrists thoroughly with product and allow to dry without wiping

Inactive ingredients

aloe vera, carbomer, D&C green #5, D&C yellow #10, fragrance, purified water, triethanolamine

PRINCIPAL DISPLAY PANEL – Sanear 0.057 fl. oz. Pouch

SaniPortables®

Instant Hand

Sanitizer

KILLS 99.9% of GERMS

FRESH SCENT

Enriched with Aloe Vera

0.057 fl. oz. (1.68 ML)

Distributed by

SANEAR Corporation

Matthews, NC 28105

PRINCIPAL DISPLAY PANEL – Sanear 25 count Box

Made in the U.S.A.

NDC 23638-1111-1

SaniPortables®

Instant Hand Sanitizer

KILLS 99.9% of GERMS

Fresh Scent

Enriched with Aloe Vera

25 packets

Each Packet .057 fl. oz. (1.68 ML)